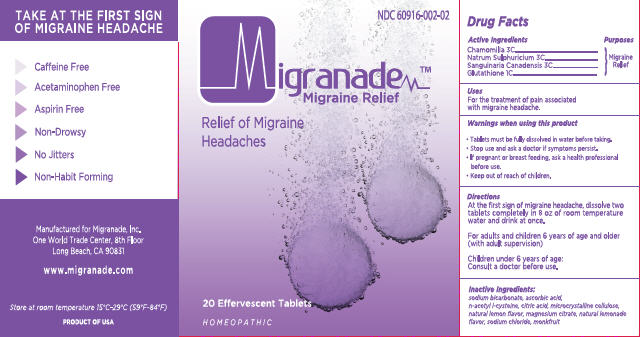 DRUG LABEL: Migranade
NDC: 60916-002 | Form: TABLET
Manufacturer: Migranade Inc.
Category: homeopathic | Type: HUMAN OTC DRUG LABEL
Date: 20140801

ACTIVE INGREDIENTS: CHAMOMILE 3 [hp_C]/3 g; SODIUM SULFATE 3 [hp_C]/3 g; SANGUINARIA CANADENSIS ROOT 3 [hp_C]/3 g; GLUTATHIONE 1 [hp_C]/3 g
INACTIVE INGREDIENTS: SODIUM BICARBONATE; ASCORBIC ACID; ACETYLCYSTEINE; CITRIC ACID MONOHYDRATE; CELLULOSE, MICROCRYSTALLINE; MAGNESIUM CITRATE; SODIUM CHLORIDE; SIRAITIA GROSVENORII FRUIT

Migranade Migraine Relief

Active Ingredients

Chamomilla 3C

Natrum Sulphuricum 3C

Sanguinaria Canadensis 3C

Glutathione 1C

Purpose

Migraine Relief

Uses

For the treatment of pain associated with migraine headache.

Warnings

- Tablets must be fully dissolved in water before taking.
- Stop use and ask a doctor if symptoms persist.
- If pregnant or breast feeding, ask a health professional before use.

Keep Out of Reach of Children

Directions

- At the first sign of migraine headache, dissolve two tablets completely in 8 oz of room temperature water and drink at once.
- For adults and children 6 years of age and older (with adult supervision)
- Children under 6 years of age: Consult a doctor before use.

Inactive Ingredients

sodium bicarbonate, ascorbic acid, n-acetyl l-cysteine, citric acid, microcrystalline cellulose, natural lemon flavor, magnesium citrate, natural lemonade flavor, sodium chloride, monkfruit

Principal Display Panel

NDC 60916-002-02

Migranade™

Migraine Relief

Relief of Migraine Headaches

20 Effervescent Tablets

Homeopathic

TAKE AT THE FIRST SIGN OF MIGRAINE HEADACHE

• Caffeine Free

• Acetaminophen Free

• Aspirin Free

• Non-Drowsy

• No Jitters

• Non-Habit Forming

Manufactured for Migranade, Inc.

One World Trade Center, 8th Floor

Long Beach, CA 90831

www.migranade.com

Store at room temperature 15°C-29C° (59F°-84°F)

Product of USA

Carton Label